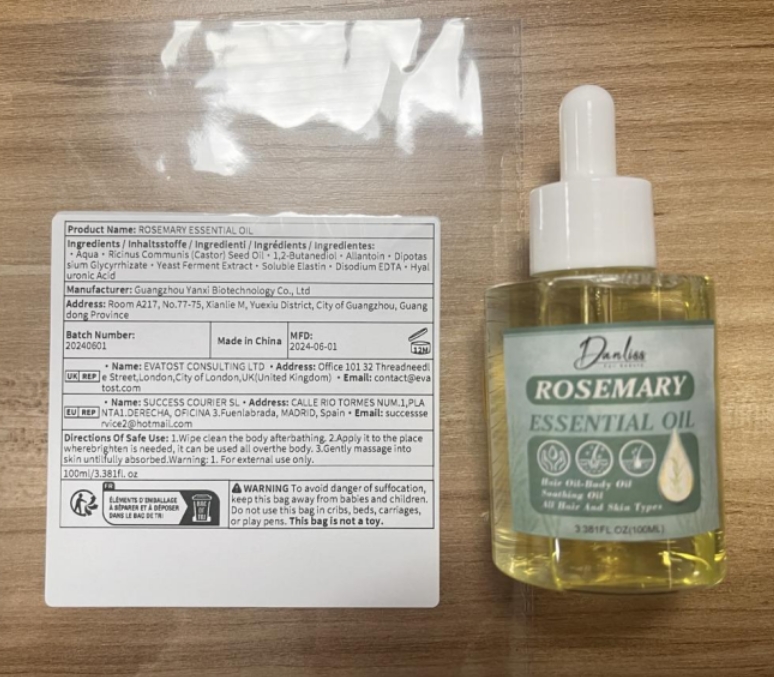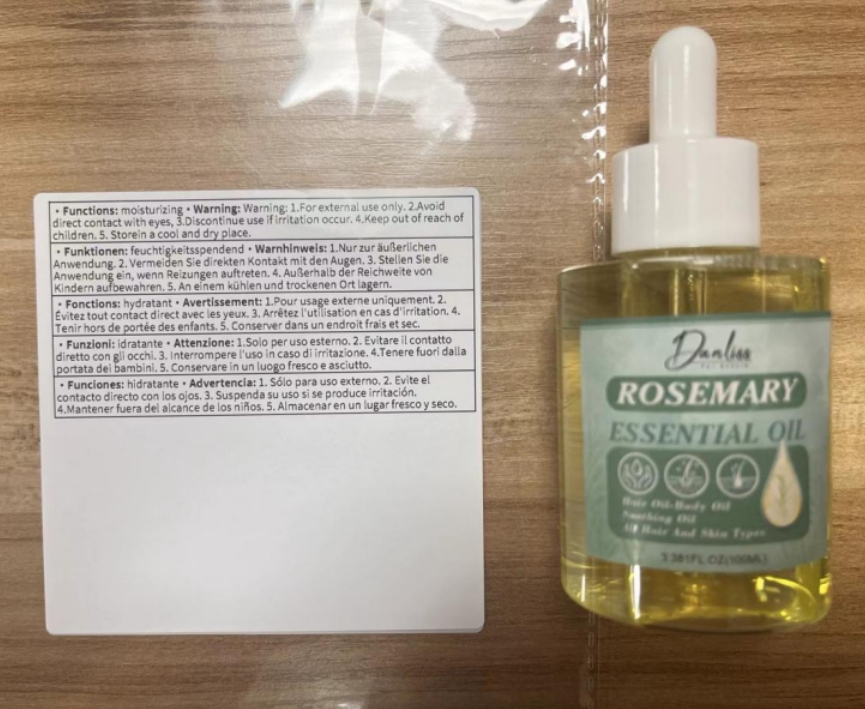 DRUG LABEL: Rosemary EssentialOil
NDC: 84025-084 | Form: OIL
Manufacturer: Guangzhou Yanxi Biotechnology Co., Ltd
Category: otc | Type: HUMAN OTC DRUG LABEL
Date: 20240723

ACTIVE INGREDIENTS: HYALURONIC ACID 3 mg/100 mL; ALLANTOIN 5 mg/100 mL
INACTIVE INGREDIENTS: WATER

DOSAGE AND ADMINISTRATION

USE AS A NORMAL HAIR CREAM

WARNINGS

keep out of childrem

INACTIVE INGREDIENT

Aqua

INDICATIONS AND USAGE

For daily hair care

keep out of childrem

PURPOSE

strong and nourishing hair